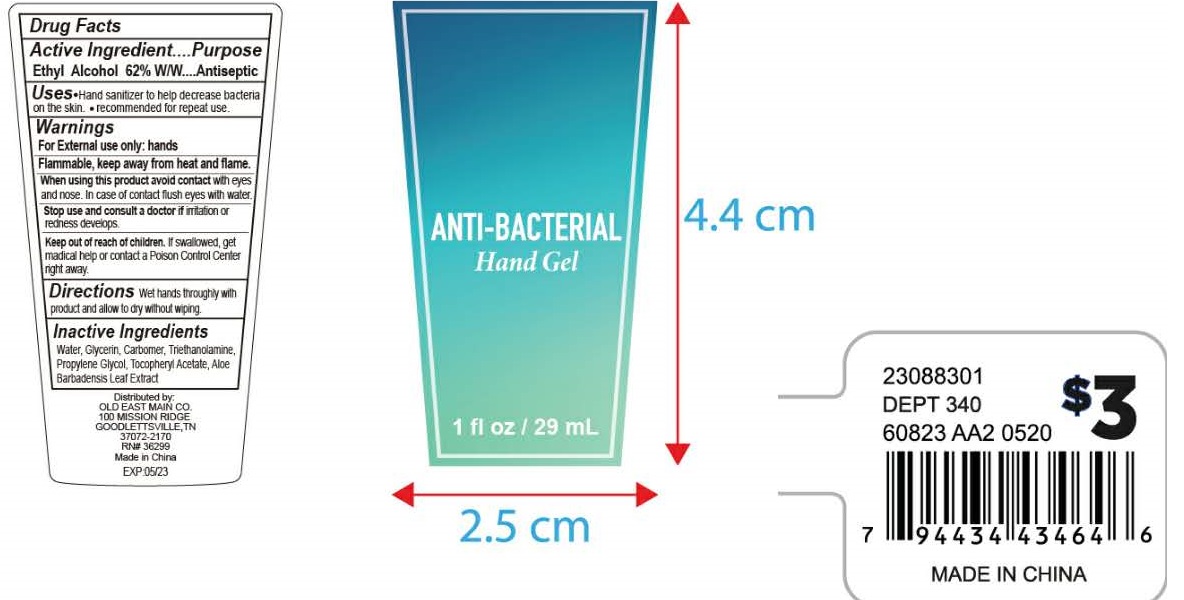 DRUG LABEL: Anti-Bacterial Hand
NDC: 74149-012 | Form: GEL
Manufacturer: Yiwu Yangjie Daily Chemicals Co.,Ltd.
Category: otc | Type: HUMAN OTC DRUG LABEL
Date: 20200416

ACTIVE INGREDIENTS: alcohol 62 mL/100 mL
INACTIVE INGREDIENTS: WATER; PROPYLENE GLYCOL; ALOE VERA LEAF; GLYCERIN; .ALPHA.-TOCOPHEROL ACETATE, D-; TROLAMINE

Drug facts

Active ingredient ................ Purpose

Ethyl Alcohol 62% W/W ... Antiseptic

PURPOSE

- Hand sanitizer to help decrease bacteria on the skin.
- recoomended for repeat use.

KEEP OUT OF REACH OF CHILDREN

If swallowed, get medical help or contact local poison control center right away.

INDICATIONS AND USAGE

Wet hands throughly with product and allow to dry without wiping.

WARNINGS

For external use only: hands.
Flammable. Keep away from heat or flame.

When using this products, avoid contact with eyes and nose. In case of contact, flush eyes with water.

Stop using and consult a doctor, if irritation and redness develops.

DOSAGE AND ADMINISTRATION

Wet hands throughly with product and allow to dry without wiping.

INACTIVE INGREDIENT

Water, Glycerin, Carbomer, Triethanolamine, Propylene Glycol, Tocopheryl Acetate, Aloe Barbadensis Leaf Extract